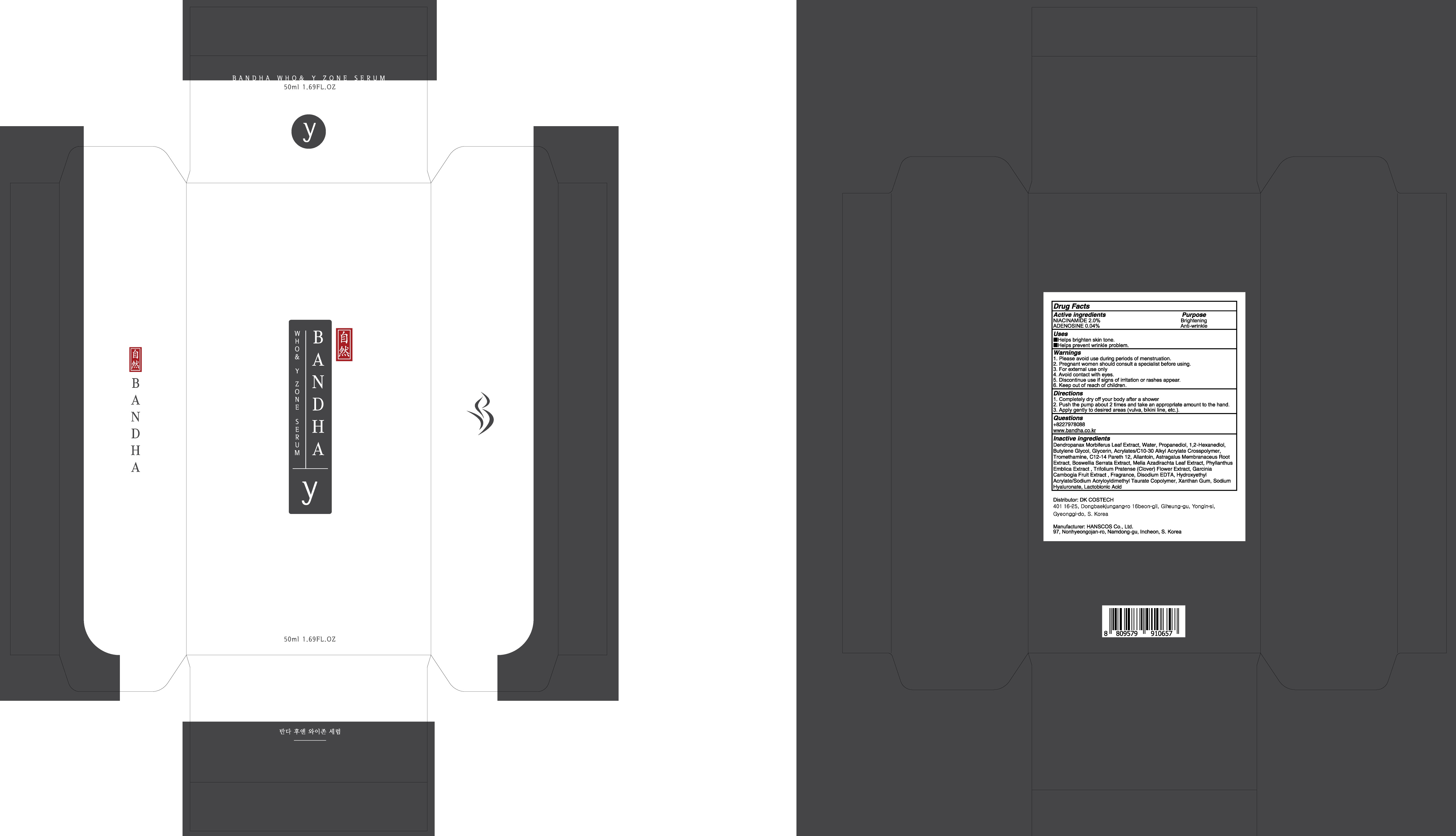 DRUG LABEL: BANDHA WHO AND Y ZONE SERUM
NDC: 80623-030 | Form: LIQUID
Manufacturer: DKCOSTECH
Category: otc | Type: HUMAN OTC DRUG LABEL
Date: 20200923

ACTIVE INGREDIENTS: NIACINAMIDE 1.0 g/50 mL; ADENOSINE 0.02 g/50 mL
INACTIVE INGREDIENTS: Water; Propanediol; 1,2-Hexanediol

ACTIVE INGREDIENTS

NIACINAMIDE 2.0%
ADENOSINE 0.04%

INACTIVE INGREDIENTS

Dendropanax Morbiferus Leaf Extract, Water, Propanediol, 1,2-Hexanediol, Butylene Glycol, Glycerin, Acrylates/C10-30 Alkyl Acrylate Crosspolymer, Tromethamine, C12-14 Pareth 12, Allantoin, Astragalus Membranaceus Root Extract, Boswellia Serrata Extract, Melia Azadirachta Leaf Extract, Phyllanthus Emblica Extract , Trifolium Pratense (Clover) Flower Extract, Garcinia Cambogia Fruit Extract , Fragrance, Disodium EDTA, Hydroxyethyl Acrylate/Sodium Acryloyldimethyl Taurate Copolymer, Xanthan Gum, Sodium Hyaluronate, Lactobionic Acid

PURPOSE

Brightening
Anti-wrinkle

WARNINGS

1. Please avoid use during periods of menstruation.
2. Pregnant women should consult a specialist before using.
3. For external use only
4. Avoid contact with eyes.
5. Discontinue use if signs of irritation or rashes appear.
6. Keep out of reach of children.

KEEP OUT OF REACH OF CHILDREN

Uses

■ Helps brighten skin tone.
■ Helps prevent wrinkle problem.

Directions

1. Completely dry off your body after a shower
2. Push the pump about 2 times and take an appropriate amount to the hand.
3. Apply gently to desired areas (vulva, bikini line, etc.).

QUESTIONS

+8227978088
www.bandha.co.kr